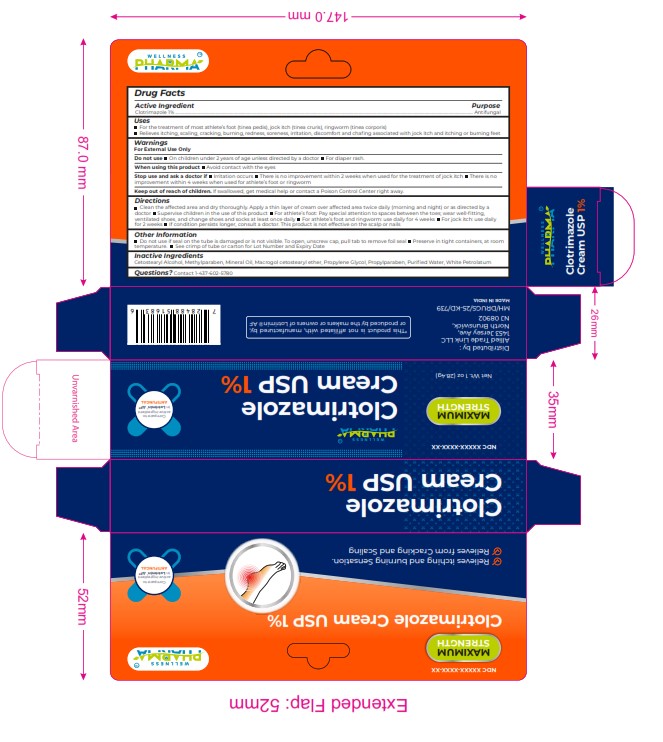 DRUG LABEL: CLOTRIMAZOLE
NDC: 84387-004 | Form: CREAM
Manufacturer: ALLIED TRADE LINK LLC
Category: otc | Type: HUMAN OTC DRUG LABEL
Date: 20241108

ACTIVE INGREDIENTS: CLOTRIMAZOLE 10 mg/1 g
INACTIVE INGREDIENTS: METHYLPARABEN; PROPYLENE GLYCOL; WHITE PETROLATUM; PROPYLPARABEN; MINERAL OIL; WATER; CETOSTEARYL ALCOHOL

CLOTRIMAZOLE

DOSAGE AND ADMISITRATION

Clotrimazole 1% ..

Clean the affected area and dry thoroughly. Apply a thin layer of cream over affected area twice daily (morning and night) or as directed by a
doctor Supervise children in the use of this product For athlete’s foot: Pay special attention to spaces between the toes; wear well-ﬁtting,
ventilated shoes, and change shoes and socks at least once daily For athlete’s foot and ringworm: use daily for 4 weeks For jock itch: use daily
for 2 weeks If condition persists longer, consult a doctor. This product is not effective on the scalp or nails

Warnings

For External Use Only
Do not use On children under 2 years of age unless directed by a doctor For diaper rash.
When using this product Avoid contact with the eyes
Stop use and ask a doctor if Irritation occurs There is no improvement within 2 weeks when used for the treatment of jock itch There is no
improvement within 4 weeks when used for athlete’s foot or ringworm

INACTIVE INGREDIENT

Cetostearyl Alcohol, Methylparaben, Mineral Oil, Macrogol cetostearyl ether, Propylene Glycol, Propylparaben, Puriﬁed Water, White Petrolatum

INDICATIONS AND USAGE

For the treatment of most athlete’s foot (tinea pedis), jock itch (tinea cruris), ringworm (tinea corporis)
Relieves itching, scaling, cracking, burning, redness, soreness, irritation, discomfort and chaﬁng associated with jock itch and itching or burning feet

Keep out of reach of children. If swallowed, get medical help or contact a Poison Control Center right away.

PURPOSE

Antifungal

WARNINGS

For External Use Only
Do not use On children under 2 years of age unless directed by a doctor For diaper rash.
When using this product Avoid contact with the eyes
Stop use and ask a doctor if Irritation occurs There is no improvement within 2 weeks when used for the treatment of jock itch There is no
improvement within 4 weeks when used for athlete’s foot or ringworm